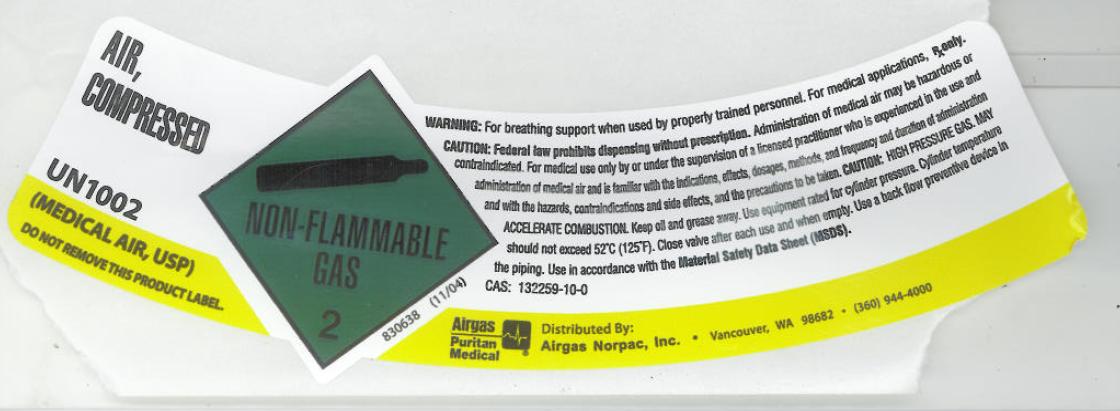 DRUG LABEL: AIR
NDC: 57472-006 | Form: GAS
Manufacturer: AIRGAS-NORPAC INC.
Category: prescription | Type: HUMAN PRESCRIPTION DRUG LABEL
Date: 20111221

ACTIVE INGREDIENTS: Air 1000 mL/1 L

Air Label

PACKAGE LABEL

AIR, COMPRESSED UN1002
(MEDICAL AIR, USP)
DO NOT REMOVE THIS PRODUCT LABEL. NON-FLAMMABLE GAS 2 830638 (11/04)
WARNING: For breathing support when used by properly trained personnel. For medical applications, Rx only.
CAUTION: Federal law prohibits dispensing without prescription.
Administration of medical air may be hazardous or contraindicated. For medical use only by or under supervision of a licensed practitioner who is experienced in the use and administration of medical air and is familiar with the indications, effects, dosages, methods, and frequency and duration of administration, and with the hazards, contraindications, and side effects and the precautions to be taken. CAUTION: HIGH PRESSURE GAS. MAY ACCELERATE COMBUSTION. Keep oil and grease away. Use equipment rated for cylinder pressure. Cylinder temperatures should not exceed 52C (125F). Close valve after each use and when empty. Use a back flow preventive device in the piping. Use in accordance with the Material Safety Data Sheet (MSDS). CAS: 132259-10-0
AIRGAS PURITAN MEDICAL Distributed By: Airgas Norpac, Inc. Vancouver, WA 98682 (360) 944-4000